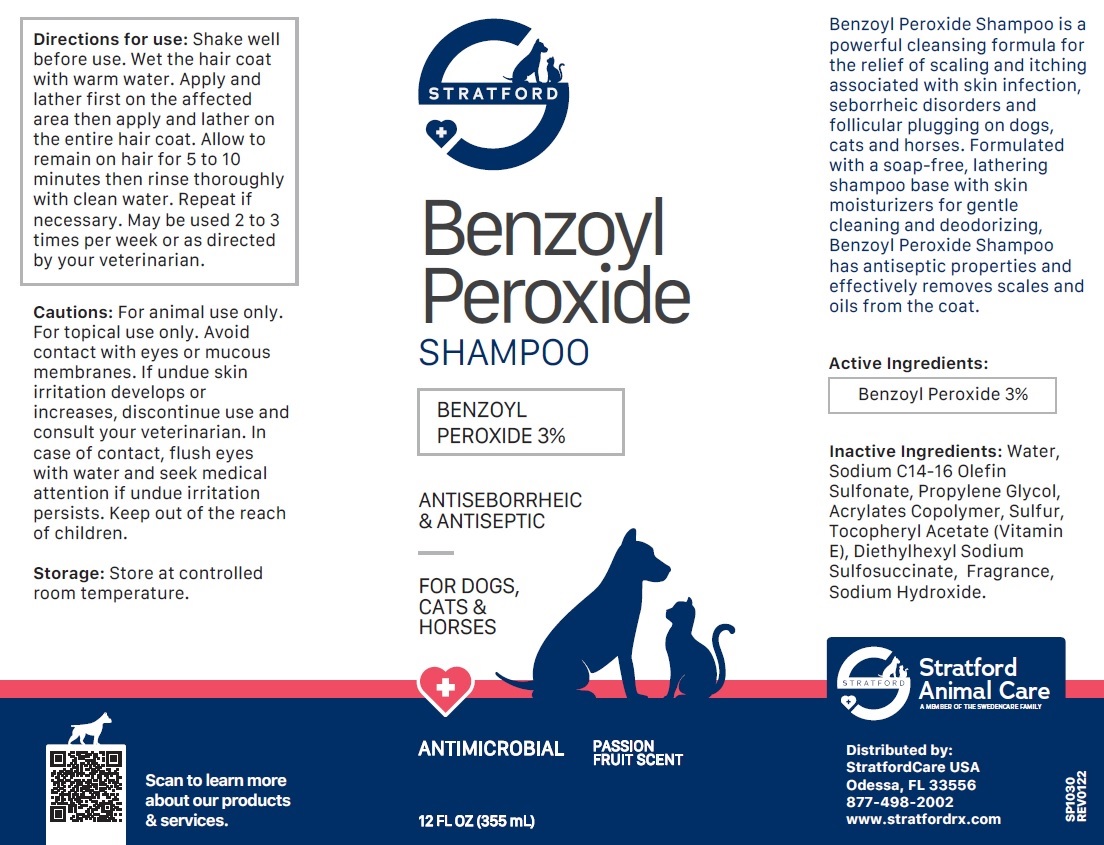 DRUG LABEL: Benzoyl Peroxide 3%
NDC: 86069-123 | Form: SHAMPOO
Manufacturer: Stratford Care Usa, Inc.
Category: animal | Type: OTC ANIMAL DRUG LABEL
Date: 20221123

ACTIVE INGREDIENTS: BENZOYL PEROXIDE 3 g/100 mL
INACTIVE INGREDIENTS: WATER; SODIUM C14-16 OLEFIN SULFONATE; PROPYLENE GLYCOL; BUTYL ACRYLATE/METHYL METHACRYLATE/METHACRYLIC ACID COPOLYMER (18000 MW); SULFUR; .ALPHA.-TOCOPHEROL ACETATE; DOCUSATE SODIUM; SODIUM HYDROXIDE

Benzoyl Peroxide SHAMPOO

Active Ingredients:

Benzoyl Peroxide 3%

PURPOSE

ANTISEBORRHEIC & ANTISEPTIC

INDICATIONS AND USAGE

Benzoyl Peroxide Shampoo is a powerful cleansing formula for the relief of scaling and itching associated with skin infection, seborrheic disorders and follicular plugging on dogs, cats and horses. Formulated with a soap-free, lathering shampoo base with skin moisturizers for gentle cleaning and deodorizing, Benzoyl Peroxide Shampoo has antiseptic properties and effectively removes scales and oils from the coat.

INACTIVE INGREDIENT

Inactive Ingredients: Water, Sodium C14-16 Olefin Sulfonate, Propylene Glycol, Acrylates Copolymer, Sulfur, Tocopheryl Acetate (Vitamin E), Diethylhexyl Sodium Sulfosuccinate, Fragrance, Sodium Hydroxide.

DOSAGE AND ADMINISTRATION

Directions for use: Shake well before use. Wet the hair coat with warm water. Apply and lather first on the affected area then apply and lather on the entire hair coat. Allow to remain on hair for 5 to 10 minutes then rinse thoroughly with clean water. Repeat if necessary. May be used 2 to 3 times per week or as directed by your veterinarian.

PRECAUTIONS

Cautions: For animal use only. For topical use only. Avoid contact with eyes or mucous membranes. If undue skin irritation develops or increases, discontinue use and consult your veterinarian. In case of contact, flush eyes with water and seek medical attention if undue irritation persists. Keep out of the reach of children.

Storage: Store at controlled room temperature.

FOR DOGS, CATS & HORSES

ANTIMICROBIAL

PASSION FRUIT SCENT

Stratford Animal Care
A MEMBER OF THE SWEDENCARE FAMILY

Distributed by:
StratfordCare USA
Odessa, FL 33556
877-498-2002
www.stratfordrx.com